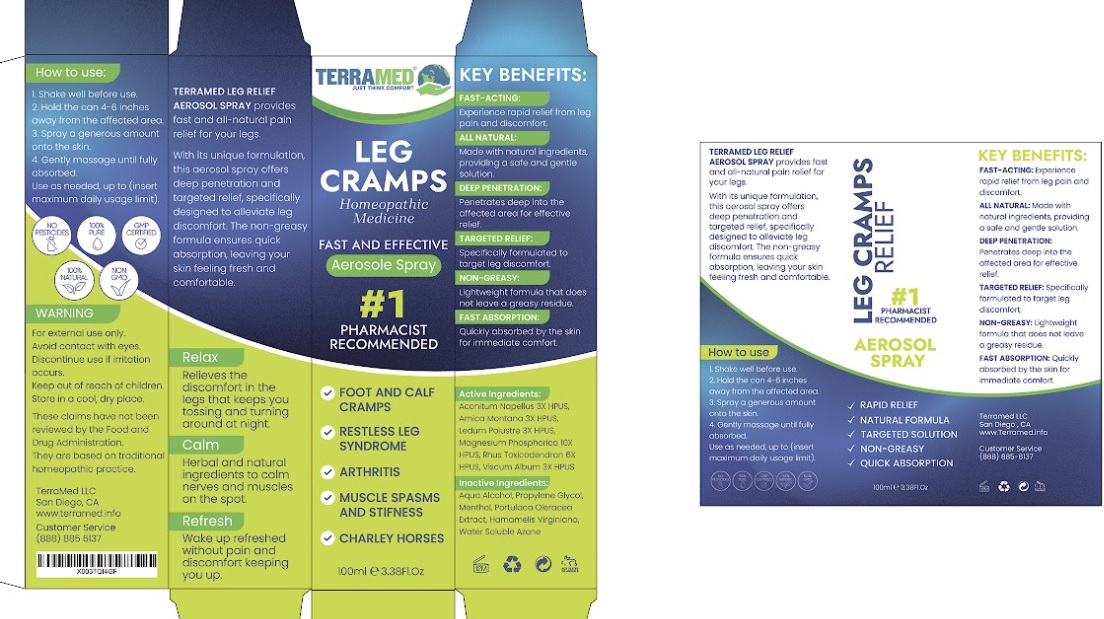 DRUG LABEL: Terramed Just Think Comfort leg cramp
NDC: 83004-007 | Form: LIQUID
Manufacturer: Rida LLC
Category: homeopathic | Type: HUMAN OTC DRUG LABEL
Date: 20250310

ACTIVE INGREDIENTS: ACONITUM NAPELLUS WHOLE 3 [hp_X]/100 mL; ARNICA MONTANA WHOLE 3 [hp_X]/100 mL; MAGNESIUM PHOSPHATE, DIBASIC TRIHYDRATE 10 [hp_X]/100 mL; TOXICODENDRON PUBESCENS LEAF 6 [hp_X]/100 mL; VISCUM ALBUM WHOLE 3 [hp_X]/100 mL
INACTIVE INGREDIENTS: WATER; MENTHOL; HAMAMELIS VIRGINIANA WHOLE; PURSLANE; PROPYLENE GLYCOL; LAUROCAPRAM

Drug Facts

Active Ingredient

Aconitum Napellus 3X HPUS

Arnica Montana 3X HPUS

Magnesium Phosphorica 10X HPUS

Rhus Toxicodendron 6X HPUS

Viscum Album 3X HPUS

Purpose

Muscle Soreness Relief

Uses

- prevents muscle cramps
- releases muscle tightness
- reduces muscle soreness

Warnings

For external use only.

If eye contact occurs, rinse thoroughly with water.

Stop use and ask a doctor if unintended effects occur.

If pregnant or breastfeeding, ask a health professional before use.

Keep out of reach of children. If swallowed, get medical help or contact a Poison Control Center right away.

Directions

- shake well
- apply 3–5 pumps onto entire muscle group(s) or area
- briskly rub in until absorbed
- use as needed
- allow to air dry

Inactive Ingredients

Aqua, Menthol, Hammamelis Virginiana, Portulaca Oleracea Extract, Propylene Glycol, Water Soluble Azone